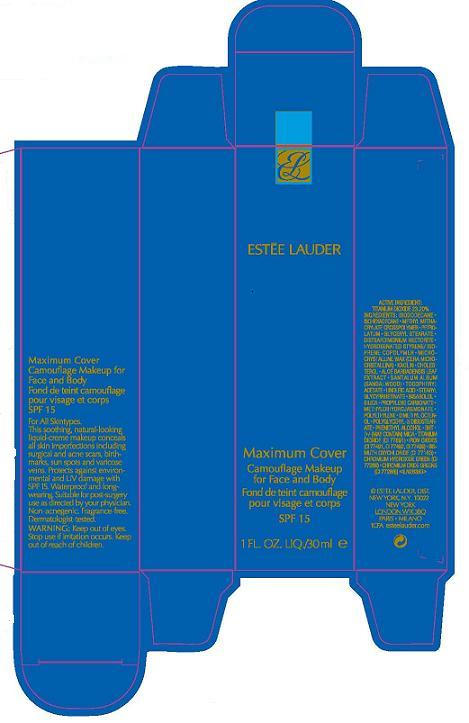 DRUG LABEL: MAXIMUM COVER CAMOUFLAGE MAKEUP
NDC: 11559-002 | Form: CREAM
Manufacturer: ESTEE LAUDER INC
Category: otc | Type: HUMAN OTC DRUG LABEL
Date: 20100406

ACTIVE INGREDIENTS: TITANIUM DIOXIDE 19.90 mL/100 mL

ACTIVE INGREDIENT: TITANIUM DIOXIDE 19.90%

WARNINGS

WARNING: KEEP OUT OF EYES. STOP USE IF IRRITATION OCCURS.

KEEP OUT OF REACH OF CHILDREN

PACKAGE LABEL

PRINCIPAL DISPLAY PANEL

ESTEE LAUDER
MAXIMUM COVER
CAMOUFLAGE MAKEUP
FOR FACE AND BODY
SPF 15

1 FL OZ/30 mL
ESTEE LAUDER DIST
NEW YORK, NY 10022
1CFA
ESTEELAUDER.COM